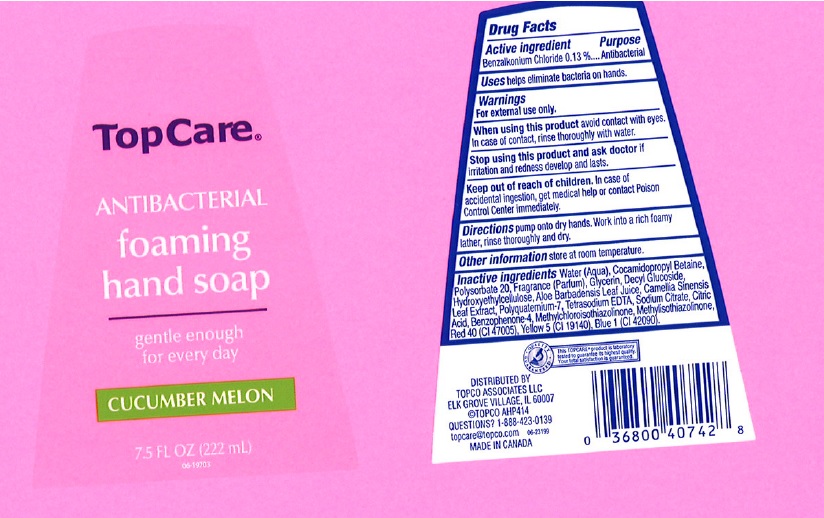 DRUG LABEL: TopCare
NDC: 36800-112 | Form: LIQUID
Manufacturer: TopCo Associates LLC
Category: otc | Type: HUMAN OTC DRUG LABEL
Date: 20170419

ACTIVE INGREDIENTS: BENZALKONIUM CHLORIDE 1.3 mg/1 mL
INACTIVE INGREDIENTS: WATER; COCAMIDOPROPYL BETAINE; POLYSORBATE 20; GLYCERIN; DECYL GLUCOSIDE; HYDROXYETHYL CELLULOSE (5000 CPS AT 1%); ALOE VERA LEAF; GREEN TEA LEAF; POLYQUATERNIUM-7 (70/30 ACRYLAMIDE/DADMAC; 1600000 MW); EDETATE SODIUM; SODIUM CITRATE; CITRIC ACID MONOHYDRATE; SULISOBENZONE; METHYLCHLOROISOTHIAZOLINONE; METHYLISOTHIAZOLINONE; FD&C YELLOW NO. 5; FD&C RED NO. 40; FD&C BLUE NO. 1

Drug Facts

Active ingredient

Benzalkonium Chloride 0.13%

Purpose

Antibacterial

Uses

helps eliminate bacteria on hands.

Warnings

For external use only.

When using this product

avoid contact with eyes. In case of contact, rinse thoroughly with water.

Stop using this product and ask doctor if

irritation or redness develop and last.

Keep out of reach of children.

In case of accidental ingestion, get medical help or contact a Poison Control Center immediately.

Directions

pump onto dry hands. Work into a rich foamy lather, rinse thoroughly and dry.

Other information

store at room temperature.

Inactive ingredients

Water (Aqua), Cocamidopropyl Betaine, Polysorbate 20, Fragrance (Parfum), Glycerin, Decyl Glucoside, Hydroxyethylcellulose, Aloe Barbadensis Leaf Juice, Camellia Sinensis Leaf Extract, Polyquaternium-7, Tetrasodium EDTA, Sodium Citrate, Citric Acid, Benzophenone-4, Methylchloroisothiazolinone, Methylisothiazolinone, Red 40 (CI 47005), Yellow 5 (CI 19140), Blue 1 (CI 42090).